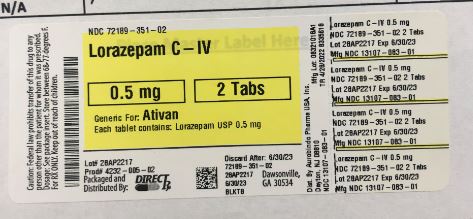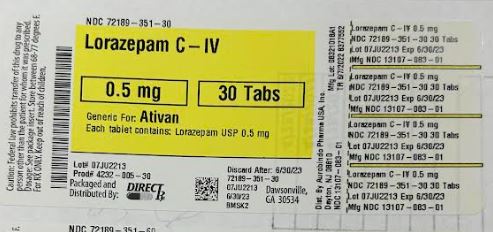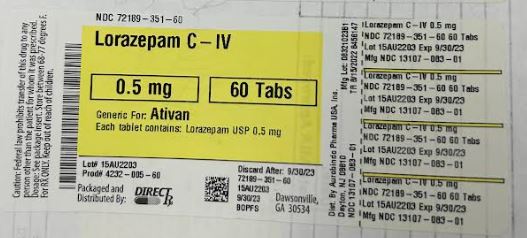 DRUG LABEL: LORAZEPAM
NDC: 72189-351 | Form: TABLET
Manufacturer: DirectRx
Category: prescription | Type: HUMAN PRESCRIPTION DRUG LABEL
Date: 20250122
DEA Schedule: CIV

ACTIVE INGREDIENTS: LORAZEPAM 0.5 mg/1 1
INACTIVE INGREDIENTS: POLACRILIN POTASSIUM; ANHYDROUS LACTOSE; MAGNESIUM STEARATE; CELLULOSE, MICROCRYSTALLINE

LORAZEPAM

DESCRIPTION

Lorazepam USP, an antianxiety agent, has the chemical formula, 7-chloro-5-(o-chlorophenyl)-1,3-dihydro-3-hydroxy-2H-1,4-benzodiazepin-2-one:

Chemical-Structure

It is a nearly white powder almost insoluble in water. Each lorazepam tablet USP, to be taken orally, contains 0.5 mg, 1 mg, or 2 mg of lorazepam USP. The inactive ingredients present are anhydrous lactose, magnesium stearate, microcrystalline cellulose, and polacriline potassium.

CLINICAL PHARMACOLOGY

Studies in healthy volunteers show that in single high doses lorazepam has a tranquilizing action on the central nervous system with no appreciable effect on the respiratory or cardiovascular systems.

Lorazepam is readily absorbed with an absolute bioavailability of 90%. Peak concentrations in plasma occur approximately 2 hours following administration. The peak plasma level of lorazepam from a 2 mg dose is approximately 20 ng/mL.

The mean half-life of unconjugated lorazepam in human plasma is about 12 hours and for its major metabolite, lorazepam glucuronide, about 18 hours. At clinically relevant concentrations, lorazepam is approximately 85% bound to plasma proteins. lorazepam is rapidly conjugated at its 3-hydroxy group into lorazepam glucuronide which is then excreted in the urine. Lorazepam glucuronide has no demonstrable central nervous system (CNS) activity in animals.

The plasma levels of lorazepam are proportional to the dose given. There is no evidence of accumulation of lorazepam on administration up to 6 months.

Studies comparing young and elderly subjects have shown that advancing age does not have a significant effect on the pharmacokinetics of lorazepam. However, in one study involving single intravenous doses of 1.5 to 3 mg of Lorazepam injection, mean total body clearance of lorazepam decreased by 20% in 15 elderly subjects of 60 to 84 years of age compared to that in 15 younger subjects of 19 to 38 years of age.

INDICATIONS AND USAGE

Lorazepam tablets are indicated for the management of anxiety disorders or for the short-term relief of the symptoms of anxiety or anxiety associated with depressive symptoms. Anxiety or tension associated with the stress of everyday life usually does not require treatment with an anxiolytic.

The effectiveness of lo razepam tablets in long-term use, that is, more than 4 months, has not been assessed by systematic clinical studies. The physician should periodically reassess the usefulness of the drug for the individual patient.

CONTRAINDICATIONS

Lorazepam is contraindicated in patients with:
• hypersensitivity to benzodiazepines or to any components of the formulation
• acute narrow-angle glaucoma.

WARNINGS

Risks from Concomitant Use with Opioids

Concomitant use of benzodiazepines, including lorazepam, and opioids may result in profound sedation, respiratory depression, coma, and death. Because of these risks, reserve concomitant prescribing of these drugs in patients for whom alternative treatment options are inadequate.

Observational studies have demonstrated that concomitant use of opioid analgesics and benzodiazepines increases the risk of drug-related mortality compared to use of opioids alone. If a decision is made to prescribe lorazepam concomitantly with opioids, prescribe the lowest effective dosages and minimum durations of concomitant use, and follow patients closely for signs and symptoms of respiratory depression and sedation. In patients already receiving an opioid analgesic, prescribe a lower initial dose of lorazepam than indicated in the absence of an opioid and titrate based on clinical response. If an opioid is initiated in a patient already taking lorazepam, prescribe a lower initial dose of the opioid and titrate based upon clinical response.

Advise both patients and caregivers about the risks of respiratory depression and sedation when lorazepam is used with opioids. Advise patients not to drive or operate heavy machinery until the effects of concomitant use with the opioid have been determined (seePRECAUTIONS: Drug Interactions).

Abuse, Misuse, and Addiction

The use of benzodiazepines, including lorazepam, exposes users to the risks of abuse, misuse, and addiction, which can lead to overdose or death. Abuse and misuse of benzodiazepines often (but not always) involve the use of doses greater than the maximum recommended dosage and commonly involve concomitant use of other medications, alcohol, and/or illicit substances, which is associated with an increased frequency of serious adverse outcomes, including respiratory depression, overdose, or death (seeDRUG ABUSE AND DEPENDENCE: Abuse).

Before prescribing lorazepam and throughout treatment, assess each patient’s risk for abuse, misuse, and addiction (e.g., using a standardized screening tool). Use of lorazepam, particularly in patients at elevated risk, necessitates counseling about the risks and proper use of lorazepam along with monitoring for signs and symptoms of abuse, misuse, and addiction. Prescribe the lowest effective dosage; avoid or minimize concomitant use of CNS depressants and other substances associated with abuse, misuse, and addiction (e.g., opioid analgesics, stimulants); and advise patients on the proper disposal of unused drug. If a substance use disorder is suspected, evaluate the patient and institute (or refer them for) early treatment, as appropriate.

Dependence and Withdrawal Reactions

To reduce the risk of withdrawal reactions, use a gradual taper to discontinue lorazepam or reduce the dosage (a patient-specific plan should be used to taper the dose)(SEE DOSAGE AND ADMINSTRATION: Discontinuation or Dosage Reduction of lorazepam).
Patients at an increased risk of withdrawal adverse reactions after benzodiazepine discontinuation or rapid dosage reduction include those who take higher dosages, and those who have had longer durations of use.

Acute Withdrawal Reactions

The continued use of benzodiazepines, including lorazepam, may lead to clinically significant physical dependence. Abrupt discontinuation or rapid dosage reduction of lorazepam after continued use, or administration of flumazenil (a benzodiazepine antagonist) may precipitate acute withdrawal reactions, which can be life-threatening (e.g., seizures)(SEE DRUG ABUSE AND DEPENDENCE: Dependence).

Protracted Withdrawal Syndrome

In some cases, benzodiazepine users have developed a protracted withdrawal syndrome with withdrawal symptoms lasting weeks to more than 12 months (SEE DRUG ABUSE AND DEPENDENCE: Dependence).
Pre-existing depression may emerge or worsen during use of benzodiazepines including lorazepam. Lorazepam is not recommended for use in patients with a primary depressive disorder or psychosis.
Use of benzodiazepines, including lorazepam, both used alone and in combination with other CNS depressants, may lead to potentially fatal respiratory depression(SEE PRECAUTIONS: Drug Interactions).

As with all patients on CNS-depressant drugs, patients receiving lorazepam should be warned not to operate dangerous machinery or motor vehicles and that their tolerance for alcohol and other CNS depressants will be diminished.

PRECAUTIONS

In patients with depression, a possibility for suicide should be borne in mind; benzodiazepines should not be used in such patients without adequate antidepressant therapy.

Lorazepam should be used with caution in patients with compromised respiratory function (e.g., COPD, sleep apnea syndrome).

Elderly or debilitated patients may be more susceptible to the sedative effects of l orazepam. Therefore, these patients should be monitored frequently and have their dosage adjusted carefully according to patient response; the initial dosage should not exceed 2 mg.

Paradoxical reactions have been occasionally reported during benzodiazepine use. Such reactions may be more likely to occur in children and the elderly. Should these occur, use of the drug should be discontinued.

The usual precautions for treating patients with impaired renal or hepatic function should be observed. As with all benzodiazepines, the use of l orazepam may worsen hepatic encephalopathy; therefore, l orazepam should be used with caution in patients with severe hepatic insufficiency and/or encephalopathy. Dosage for patients with severe hepatic insufficiency should be adjusted carefully according to patient response; lower doses may be sufficient in such patients.

In patients where gastrointestinal or cardiovascular disorders coexist with anxiety, it should be noted that l orazepam has not been shown to be of significant benefit in treating the gastrointestinal or cardiovascular component.

Esophageal dilation occurred in rats treated with l orazepam for more than 1 year at 6 mg/kg/day. The no- effect dose was 1.25 mg/kg/day (approximately 6 times the maximum human therapeutic dose of 10 mg/day). The effect was reversible only when the treatment was withdrawn within 2 months of first observation of the phenomenon. The clinical significance of this is unknown. However, use of l orazepam for prolonged periods and in geriatric patients requires caution, and there should be frequent monitoring for symptoms of upper GI disease.

Safety and effectiveness of l orazepam in children of less than 12 years have not been established.

Information for Patients

Advise the patient to read the FDA-approved patient labeling (Medication Guide).

Risks from Concomitant Use with Opioids
Advise both patients and caregivers about the risks of potentially fatal respiratory depression and sedation when lorazepam is used with opioids and not to use such drugs concomitantly unless supervised by a health care provider. Advise patients not to drive or operate heavy machinery until the effects of concomitant use with the opioid have been determined (SEE WARNINGS: Risks from Concomitant Use of Opioids and PRECAUTIONS: Drug Interactions).

Abuse, Misuse, and Addiction
Inform patients that the use of lorazepam even at recommended doses, exposes users to risks of abuse, misuse, and addiction, which can lead to overdose and death, especially when used in combination with other medications (e.g., opioid analgesics), alcohol, and/or illicit substances. Inform patients about the signs and symptoms of benzodiazepine abuse, misuse, and addiction; to seek medical help if they develop these signs and/or symptoms; and on the proper disposal of unused drug (SEE WARNINGS: Abuse Misuse, and Addiction and DRUG ABUSE AND DEPENDENCE).

Withdrawal Reactions
Inform patients that the continued use of lorazepam may lead to clinically significant physical dependence and that abrupt discontinuation or rapid dosage reduction of lorazepam may precipitate acute withdrawal reactions, which can be life-threatening. Inform patients that in some cases, patients taking benzodiazepines have developed a protracted withdrawal syndrome with withdrawal symptoms lasting weeks to more than 12 months. Instruct patients that discontinuation or dosage reduction of lorazepam may require a slow taper (see WARNINGS:Dependence and Withdrawal Reactions and DRUG ABUSE AND DEPENDENCE).

Essential Laboratory Tests
Some patients on l orazepam have developed leukopenia, and some have had elevations of LDH. As with other benzodiazepines, periodic blood counts and liver function tests are recommended for patients on long-term therapy.

Drug Interactions

The concomitant use of benzodiazepines and opioids increases the risk of respiratory depression because of actions at different receptor sites in the CNS that control respiration. Benzodiazepines interact at GABAA sites and opioids interact primarily at mu receptors. When benzodiazepines and opioids are combined, the potential for benzodiazepines to significantly worsen opioid-related respiratory depression exists. Limit dosage and duration of concomitant use of benzodiazepines and opioids and monitor patients closely for respiratory depression and sedation.

The benzodiazepines, including lorazepam, produce increased CNS-depressant effects when administered with other CNS depressants such as alcohol, barbiturates, antipsychotics, sedative/hypnotics, anxiolytics, antidepressants, narcotic analgesics, sedative antihistamines, anticonvulsants, and anesthetics.

Concomitant use of clozapine and lorazepam may produce marked sedation, excessive salivation, hypotension, ataxia, delirium, and respiratory arrest.

Concurrent administration of lorazepam with valproate results in increased plasma concentrations and reduced clearance of lorazepam. lorazepam dosage should be reduced to approximately 50% when coadministered with valproate.

Concurrent administration of lorazepam with probenecid may result in a more rapid onset or prolonged effect of lorazepam due to increased half-life and decreased total clearance. Lorazepam dosage needs to be reduced by approximately 50% when coadministered with probenecid.

The effects of probenecid and valproate on lorazepam may be due to inhibition of glucuronidation.

Administration of theophylline or aminophylline may reduce the sedative effects of benzodiazepines, including lorazepam.

Carcinogenesis and Mutagenesis

No evidence of carcinogenic potential emerged in rats during an 18-month study with l orazepam. No studies regarding mutagenesis have been performed.

Pregnancy

Reproductive studies in animals were performed in mice, rats, and two strains of rabbits. Occasional anomalies (reduction of tarsals, tibia, metatarsals, malrotated limbs, gastroschisis, malformed skull, and microphthalmia) were seen in drug-treated rabbits without relationship to dosage. Although all of these anomalies were not present in the concurrent control group, they have been reported to occur randomly in historical controls. At doses of 40 mg/kg and higher, there was evidence of fetal resorption and increased fetal loss in rabbits which was not seen at lower doses.

The clinical significance of the above findings is not known. However, an increased risk of congenital malformations associated with the use of minor tranquilizers (chlordiazepoxide, diazepam, and meprobamate) during the first trimester of pregnancy has been suggested in several studies. Because the use of these drugs is rarely a matter of urgency, the use of l orazepam during this period should be avoided. The possibility that a woman of childbearing potential may be pregnant at the time of institution of therapy should be considered. Patients should be advised that if they become pregnant, they should communicate with their physician about the desirability of discontinuing the drug.

In humans, blood levels obtained from umbilical cord blood indicate placental transfer of l orazepam and l orazepam glucuronide. Infants of mothers who ingested benzodiazepines for several weeks or more preceding delivery have been reported to have withdrawal symptoms during the postnatal period.
Symptoms such as hypoactivity, hypotonia, hypothermia, respiratory depression, apnea, feeding problems, and impaired metabolic response to cold stress have been reported in neonates born of mothers who have received benzodiazepines during the late phase of pregnancy or at delivery.

Nursing Mothers

Lorazepam has been detected in human breast milk; therefore, it should not be administered to breast feeding women, unless the expected benefit to the woman outweighs the potential risk to the infant.

Sedation and inability to suckle have occurred in neonates of lactating mothers taking benzodiazepines. Infants of lactating mothers should be observed for pharmacological effects (including sedation and irritability).

Geriatric Use

Clinical studies of lorazepam generally were not adequate to determine whether subjects aged 65 and over respond differently than younger subjects; however, the incidence of sedation and unsteadiness was observed to increase with age (SEE ADVERSE REACTIONS).

Age does not appear to have a significant effect on lorazepam kinetics (SEE CLINICAL PHARMACOLOGY).

Clinical circumstances, some of which may be more common in the elderly, such as hepatic or renal impairment, should be considered. Greater sensitivity (e.g., sedation) of some older individuals cannot be ruled out. In general, dose selection for an elderly patient should be cautious, and lower doses may be sufficient in these patients(SEE DOSAGE AND ADMINISTRATION).

ADVERSE REACTIONS

Most adverse reactions to benzodiazepines, including CNS effects and respiratory depression, are dose dependent, with more severe effects occurring with high doses.
In a sample of about 3500 patients treated for anxiety, the most frequent adverse reaction to l orazepam was sedation (15.9%), followed by dizziness (6.9%), weakness (4.2%), and unsteadiness (3.4%). The incidence of sedation and unsteadiness increased with age.
Other adverse reactions to benzodiazepines, including l orazepam are fatigue, drowsiness, amnesia, memory impairment, confusion, disorientation, depression, unmasking of depression, disinhibition, euphoria, suicidal ideation/attempt, ataxia, asthenia, extrapyramidal symptoms, convulsions/seizures, tremor, vertigo, eye function/visual disturbance (including diplopia and blurred vision), dysarthria/slurred speech, change in libido, impotence, decreased orgasm; headache, coma; respiratory depression, apnea, worsening of sleep apnea, worsening of obstructive pulmonary disease; gastrointestinal symptoms including nausea, change in appetite, constipation, jaundice, increase in bilirubin, increase in liver transaminases, increase in alkaline phosphatase; hypersensitivity reactions, anaphylactoid reactions; dermatological symptoms, allergic skin reactions, alopecia; syndrome of inappropriate antidiuretic hormone (SIADH), hyponatremia; thrombocytopenia, agranulocytosis, pancytopenia; hypothermia; and autonomic manifestations.
Paradoxical reactions, including anxiety, excitation, agitation, hostility, aggression, rage, sleep disturbances/insomnia, sexual arousal, and hallucinations may occur. Small decreases in blood pressure and hypotension may occur but are usually not clinically significant, probably being related to the relief of anxiety produced by l orazepam.
To report SUSPECTED ADVERSE REACTIONS, contact Aurobindo Pharma USA, Inc. at 1-866-850-2876 or FDA at 1-800-FDA-1088 or www.fda.gov/medwatch.

DRUG ABUSE AND DEPENDENCE

Controlled Substance
Lorazepam tablets contains l orazepam, a Schedule IV controlled substance.

Abuse

Lorazepam is a benzodiazepine and a CNS depressant with a potential for abuse and addiction. Abuse is the intentional, non-therapeutic use of a drug, even once, for its desirable psychological or physiological effects. Misuse is the intentional use, for therapeutic purposes, of a drug by an individual in a way other than prescribed by a health care provider or for whom it was not prescribed. Drug addiction is a cluster of behavioral, cognitive, and physiological phenomena that may include a strong desire to take the drug, difficulties in controlling drug use (e.g., continuing drug use despite harmful consequences, giving a higher priority to drug use than other activities and obligations), and possible tolerance or physical dependence. Even taking benzodiazepines as prescribed may put patients at risk for abuse and misuse of their medication. Abuse and misuse of benzodiazepines may lead to addiction.

Abuse and misuse of benzodiazepines often (but not always) involve the use of doses greater than the maximum recommended dosage and commonly involve concomitant use of other medications, alcohol, and/or illicit substances, which is associated with an increased frequency of serious adverse outcomes, including respiratory depression, overdose, or death. Benzodiazepines are often sought by individuals who abuse drugs and other substances, and by individuals with addictive disorders (SEE WARNINGS: Abuse, Misuse, and Addiction).

The following adverse reactions have occurred with benzodiazepine abuse and/or misuse: abdominal pain, amnesia, anorexia, anxiety, aggression, ataxia, blurred vision, confusion, depression, disinhibition, disorientation, dizziness, euphoria, impaired concentration and memory, indigestion, irritability, muscle pain, slurred speech, tremors, and vertigo.

The following severe adverse reactions have occurred with benzodiazepine abuse and/or misuse: delirium, paranoia, suicidal ideation and behavior, seizures, coma, breathing difficulty, and death. Death is more often associated with polysubstance use (especially benzodiazepines with other CNS depressants such as opioids and alcohol).

Dependence
Physical Dependence
Lorazepam may produce physical dependence from continued therapy. Physical dependence is a state that develops as a result of physiological adaptation in response to repeated drug use, manifested by withdrawal signs and symptoms after abrupt discontinuation or a significant dose reduction of a drug. Abrupt discontinuation or rapid dosage reduction of benzodiazepines or administration of flumazenil, a benzodiazepine antagonist, may precipitate acute withdrawal reactions, including seizures, which can be life-threatening. Patients at an increased risk of withdrawal adverse reactions after benzodiazepine discontinuation or rapid dosage reduction include those who take higher dosages (i.e., higher and/or more frequent doses) and those who have had longer durations of use (SEE WARNINGS: Dependence and Withdrawal Reactions).

To reduce the risk of withdrawal reactions, use a gradual taper to discontinue lorazepam or reduce the dosage (see DOSAGE AND ADMINISTRATION: Discontinuation or Dosage Reduction of Lorazepam and WARNINGS).

Acute Withdrawal Signs and Symptoms
Acute withdrawal signs and symptoms associated with benzodiazepines have included abnormal involuntary movements, anxiety, blurred vision, depersonalization, depression, derealization, dizziness, fatigue, gastrointestinal adverse reactions (e.g., nausea, vomiting, diarrhea, weight loss, decreased appetite), headache, hyperacusis, hypertension, irritability, insomnia, memory impairment,muscle pain and stiffness, panic attacks, photophobia, restlessness, tachycardia, and tremor. More severe acute withdrawal signs and symptoms, including life-threatening reactions, have included catatonia, convulsions, delirium tremens, depression, hallucinations, mania, psychosis, seizures and suicidality.

Protracted Withdrawal Syndrome
Protracted withdrawal syndrome associated with benzodiazepines is characterized by anxiety, cognitive impairment, depression, insomnia, formication, motor symptoms (e.g., weakness, tremor, muscle twitches), paresthesia, and tinnitus that persists beyond 4 to 6 weeks after initial benzodiazepine withdrawal. Protracted withdrawal symptoms may last weeks to more than 12 months. As a result, there may be difficulty in differentiating withdrawal symptoms from potential re emergence or continuation of symptoms for which the benzodiazepine was being used.

Tolerance
Tolerance to lorazepam may develop from continued therapy. Tolerance is a physiological state characterized by a reduced response to a drug after repeated administration (i.e., a higher dose of a drug is required to produce the same effect that was once obtained at a lower dose). Tolerance to the therapeutic effect of lorazepam may develop; however, little tolerance develops to the amnestic reactions and other cognitive impairments caused by benzodiazepines.

OVERDOSAGE

In postmarketing experience, overdose with lorazepam has occurred predominantly in combination with alcohol and/or other drugs. Therefore, in the management of overdosage, it should be borne in mind that multiple agents may have been taken.

Symptoms
Overdosage of benzodiazepines is usually manifested by varying degrees of CNS depression ranging from drowsiness to coma. In mild cases, symptoms include drowsiness, mental confusion, paradoxical reactions, dysarthria, and lethargy. In more serious cases, and especially when other drugs or alcohol were ingested, symptoms may include ataxia, hypotonia, hypotension, cardiovascular depression, respiratory depression, hypnotic state, coma, and death.

Management
General supportive and symptomatic measures are recommended; vital signs must be monitored, and the patient closely observed. When there is a risk of aspiration, induction of emesis is not recommended.
Gastric lavage may be indicated if performed soon after ingestion or in symptomatic patients. Administration of activated charcoal may also limit drug absorption. Hypotension, though unlikely, usually may be controlled with norepinephrine bitartrate injection. Lorazepam is poorly dialyzable. Lorazepam glucuronide, the inactive metabolite, may be highly dialyzable.

The benzodiazepine antagonist flumazenil may be used in hospitalized patients as an adjunct to, not as a substitute for, proper management of benzodiazepine overdose. The prescriber should be aware of a risk of seizure in association with flumazenil treatment, particularly in long-term benzodiazepine users and in cyclic antidepressant overdose. The complete flumazenil package insert including CONTRAINDICATIONS, WARNINGS, and PRECAUTIONS sections should be consulted prior to use.

DOSAGE AND ADMINISTRATION

Lorazepam tablets are administered orally. For optimal results, dose, frequency of administration, and duration of therapy should be individualized according to patient response. To facilitate this, 0.5 mg, 1 mg, and 2 mg tablets are available.

The usual range is 2 to 6 mg/day given in divided doses, the largest dose being taken before bedtime, but the daily dosage may vary from 1 to 10 mg/day.

For anxiety, most patients require an initial dose of 2 to 3 mg/day given two times a day or three times a day.

For insomnia due to anxiety or transient situational stress, a single daily dose of 2 to 4 mg may be given, usually at bedtime.

For elderly or debilitated patients, an initial dosage of 1 to 2 mg/day in divided doses is recommended, to be adjusted as needed and tolerated.

The dosage of l orazepam tablets should be increased gradually when needed to help avoid adverse effects. When higher dosage is indicated, the evening dose should be increased before the daytime doses.

Discontinuation or Dosage Reduction of Lorazepam Tablets

To reduce the risk of withdrawal reactions, use a gradual taper to discontinue lorazepam tablets or reduce the dosage. If a patient develops withdrawal reactions, consider pausing the taper or increasing the dosage to the previous tapered dosage level. Subsequently decrease the dosage more slowly (see WARNINGS: Dependence and Withdrawal Reactions and DRUG ABUSE AND DEPENDENCE: Dependence).

HOW SUPPLIED

Lorazepam Tablets, USP are available in the following dosage strengths:
0.5 mg, white to off-while, round, flat-faced beveled edge tablets debossed with “U32” on one side and plain on the other side.
NDC 13107-083-11 Bottles of 10 tablets
NDC 13107-083-01 Bottles of 100 tablets
NDC 13107-083-05 Bottles of 500 tablets
NDC 13107-083-99 Bottles of 1000 tablets
1 mg, white to off-white, round, flat-faced beveled edge tablets debossed with “U33” on one side and bisect on the other side.

NDC 13107-084-11 Bottles of 10 tablets
NDC 13107-084-01 Bottles of 100 tablets
NDC 13107-084-05 Bottles of 500 tablets
NDC 13107-084-99 Bottles of 1000 tablets
2 mg, while to off-white, round, flat-faced beveled edge tablets debossed with a bisect separating “U” and “34” on one side and “2” on the other side.

NDC 13107-085-11 Bottles of 10 tablets
NDC 13107-085-01 Bottles of 100 tablets
NDC 13107-085-05 Bottles of 500 tablets
NDC 13107-085-99 Bottles of 1000 tablets

Keep bottles tightly closed.
Keep out of reach of children.

STORE AT 20°C to 25°C (68° to 77°F) [SEE USP CONTROLLED ROOM TEMPERATURE].

DISPENSE IN A TIGHT, LIGHT-RESISTANT CONTAINER AS DESCRIBED IN THE USP.

Dispense with Medication Guide available at www.aurobindousa.com/medication-guides

Distributed by:
Aurobindo Pharma USA, Inc.
279 Princeton-Hightstown Road
East Windsor, NJ 08520

Revised: 01/2022

MEDICATION GUIDE
LORAZEPAM Tablets, USP CIV
What is the most important information I should know about LORAZEPAM?
· LORAZEPAM isa benzodiazepine medicine. Taking benzodiazepines with opioid medicines, alcohol, or other central nervous system depressants (including street drugs) can cause severe drowsiness, breathing problems (respiratory depression), coma and death. Getemergencyhelpright away if any of the following happens:
shallow or slowedbreathing
breathingstops(whichmaylead to the heartstopping)
excessivesleepiness(sedation)
Do not drive or operate heavy machinery until you know how taking LORAZEPAM with opioids affects you.
Risk of abuse,misuse, and addiction.There is a risk of abuse,misuse,andaddictionwithbenzodiazepinesincludingLORAZEPAM whichcanlead to overdoseandserioussideeffects including comaanddeath.
Serioussideeffects including comaanddeathhavehappened in peoplewho have abused or misusedbenzodiazepines,includingLORAZEPAM.Theseserioussideeffectsmayalsoincludedelirium,paranoia,suicidalthoughts or actions,seizures,anddifficultybreathing.Call your healthcareprovider or go to thenearest hospital emergencyroomrightaway if you getany of theseserioussideeffects.
Youcandevelop an addictioneven if you take LORAZEPAM exactly as prescribed by your healthcareprovider.
TakeLORAZEPAM exactly as your healthcareproviderprescribed.
Do not share your LORAZEPAM withotherpeople.
Keep LORAZEPAM in a safeplaceandaway from children.
Physicaldependence and withdrawalreactions.LORAZEPAM cancausephysicaldependenceandwithdrawalreactions.
Do not suddenlystoptakingLORAZEPAM. StoppingLORAZEPAM suddenlycancauseseriousandlife-threateningsideeffects,including,unusualmovements,responses or expressions,seizures,suddenandseveremental or nervoussystemchanges,depression,seeing or hearingthingsthatothersdo not see or hear,anextremeincrease in activity or talking,losingtouchwithreality,andsuicidalthoughts or actions.Callyourhealthcareprovider or go to the nearest hospital emergencyroomrightaway if youget any of thesesymptoms.
Somepeoplewhosuddenlystopbenzodiazepines have symptoms that canlast for severalweeks to more than 12 months,includinganxiety,troubleremembering,learning, or concentrating,depression,problemssleeping,feelinglikeinsectsarecrawlingunder your skin,weakness,shaking,muscletwitching,burning or pricklingfeeling in your hands,arms,legs or feet, and ringing in your ears.
Physicaldependence is not the sameas drug addiction.Yourhealthcareprovidercantell you moreabout the differencesbetweenphysicaldependenceand drug addiction.
Do not takemore LORAZEPAM than prescribed or takeLORAZEPAM for longerthanprescribed.
What is LORAZEPAM?
LORAZEPAM is a prescriptionmedicineused:
to treatanxietydisorders
for the short-termrelief of the symptoms of anxiety or anxietythatcanhappenwith symptoms of depression
LORAZEPAM is a federalcontrolledsubstance(CIV)because it contains Lorazepam thatcan be abused or lead to dependence.KeepLORAZEPAM in a safeplace to preventmisuseandabuse.Selling or givingawayLORAZEPAM may harm others, and is againstthelaw.Tell your healthcareprovider if youhaveabused or beendependent on alcohol,prescriptionmedicines or streetdrugs.
It is not known if LORAZEPAM issafeandeffective for use in childrenlessthan 12 years of age.
It is not known if LORAZEPAM issafeandeffective for use for longerthan 4 months.
Donot take LORAZEPAM if you:
areallergic to Lorazepam, other benzodiazepines, or any of the ingredients in LORAZEPAM. See the end of this MedicationGuidefor a completelist of ingredients in LORAZEPAM.
Beforeyou take LORAZEPAM, tell your healthcare provider about all of your medical conditions, including if you:
have or havehaddepression,moodproblems, or suicidalthoughts or behavior
have a history of drug or alcoholabuse or addiction
have lung disease or breathingproblems(suchasCOPD,sleepapneasyndrome)
haveliver or kidneyproblems
have or havehadseizures
arepregnant or plan to becomepregnant.LORAZEPAM mayharm your unbornbaby.Youand your healthcare provider shoulddecide if you shouldtakeLORAZEPAM while you arepregnant.
arebreastfeeding or plan to breastfeed.LORAZEPAM passes into your breastmilkandmayharm your baby.Talkto your healthcareprovideraboutthebestway to feed your baby if you takeLORAZEPAM.YoushouldnotbreastfeedwhiletakingLORAZEPAM.
Tellyour healthcare provider about all the medicines you take,includingprescriptionandoverthe-countermedicines,vitamins,andherbalsupplements.
TakingLORAZEPAM withcertainothermedicinescancausesideeffectsor affect how well LORAZEPAM or the other medicines work. Do not start or stop other medicines without talking to your healthcare provider.
HowshouldI take LORAZEPAM?
TakeLORAZEPAM exactlyas your healthcareprovidertells you totake it. Yourhealthcareproviderwilltell you how muchLORAZEPAM to take andwhentotake it.
If you taketoomuchLORAZEPAM,call your healthcareprovider or go to the nearesthospitalemergency room right away.
What are the possible side effects of LORAZEPAM?
LORAZEPAM may cause serious side effects, including:
· See“What is the most important information I should know about LORAZEPAM?”
LORAZEPAM can make you sleepy or dizzy and canslow your thinking and motorskills.
Do not drive,operateheavymachinery,or do otherdangerousactivities until you know how LORAZEPAM affects you.
Do not drinkalcohol or takeother drugs that maymake you sleepy or dizzy while taking LORAZEPAM withoutfirst talking to your healthcareprovider.Whentakenwithalcohol or drugsthatcausesleepiness or dizziness,LORAZEPAM maymake your sleepiness or dizzinessmuchworse.
Depression.Pre-existingdepressionmayemerge or worsenduringuse of benzodiazepinesincludingLORAZEPAM.
The most common side effects of LORAZEPAM include:
• sedation • dizziness
• weakness • unsteadiness
These are not all the possible side effects of LORAZEPAM. Call your doctor for medical advice about side effects. You may report side effects to FDA at 1-800-FDA-1088.
How should I store LORAZEPAM?
Store LORAZEPAM in a tightly closed container at room temperature between 68°F to 77°F (20°C to 25°C).
Keep LORAZEPAM and all medicines out of the reach of children.
General information about the safe and effective use of LORAZEPAM
Medicines are sometimes prescribed for purposes other than those listed in a Medication Guide. Do not use LORAZEPAM for a condition for which it was not prescribed. Do not give LORAZEPAM to other people, even if they have the same symptoms that you have. It may harm them. You can ask your pharmacist or healthcare provider for information about LORAZEPAM that is written for health professionals.
What are the ingredients in LORAZEPAM?
Active ingredient: lorazepam
Inactive ingredients: anhydrous lactose, magnesium stearate, microcrystalline cellulose, and polacrilin potassium.
Dispense with Medication Guide available at: www.aurobindousa.com/medication-guides
Distributed by:
Aurobindo Pharma USA, Inc.
279 Princeton-Hightstown Road
East Windsor, NJ 08520
This Medication Guide has been approved by the U.S. Food and Drug Administration
Revised: 01/2022